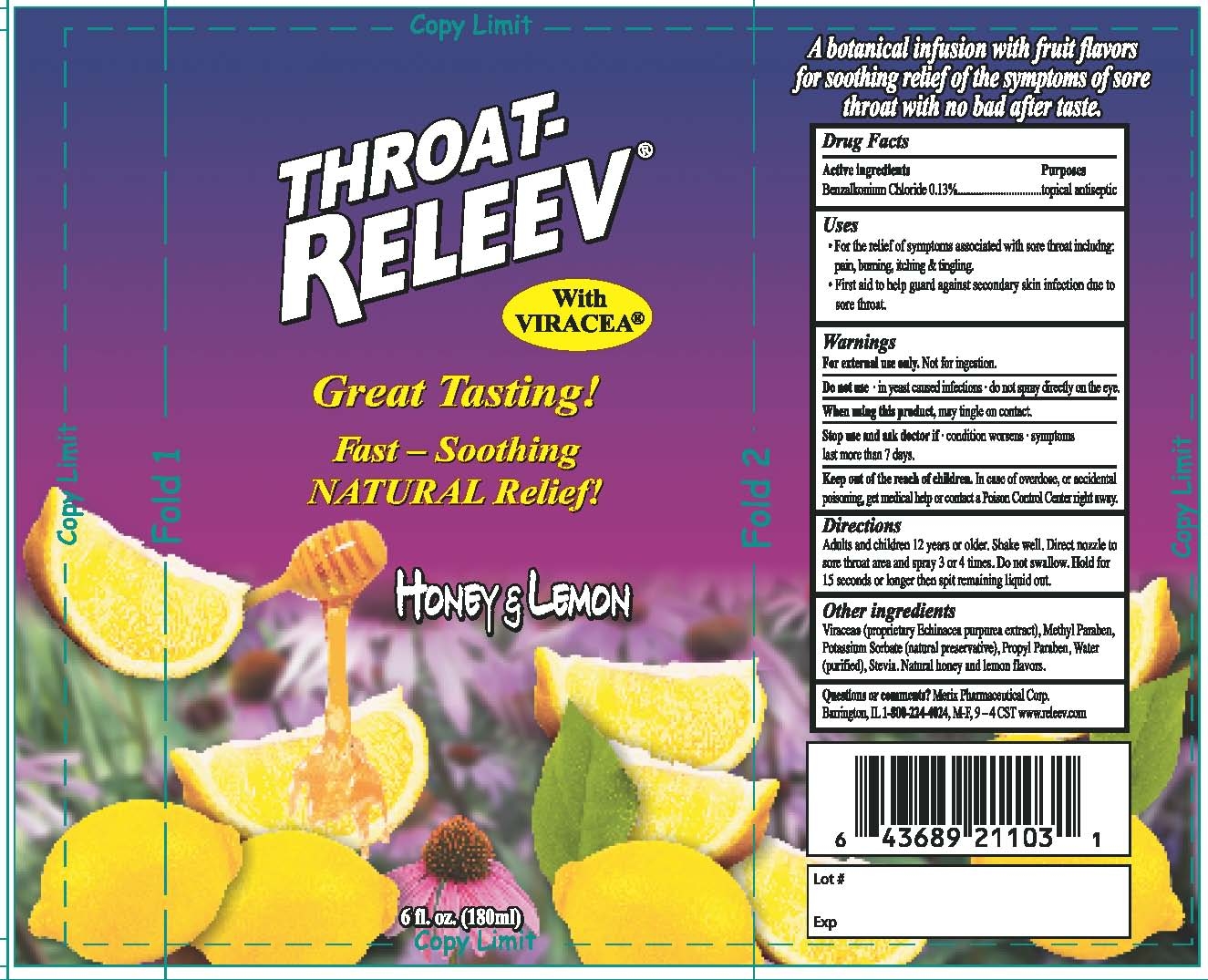 DRUG LABEL: Throat-Releev (Honey and Lemon)
NDC: 63287-211 | Form: LIQUID
Manufacturer: Merix Pharmaceutical Corp.
Category: otc | Type: HUMAN OTC DRUG LABEL
Date: 20120410

ACTIVE INGREDIENTS: Benzalkonium Chloride 1.3 mg/1 mL
INACTIVE INGREDIENTS: Water; Methylparaben; Potassium Sorbate; Propylparaben; Echinacea purpurea flowering top; STEVIA LEAF

DRUGS FACTS

ACTIVE INGREDIENTS

Benzalkonium Chloride

USES:

- For the relive of symtoms associated with sore throat including:

pain, Burning, Itching and tingling

- First aid to help guard against secondary skin infection due to sore
  throat.

WARNINGS:

For external used only. Not for ingestion.

Do not used- in yeast infections- do not spray directly on the eyes

When using this product, may tingle on contact.

Stop used and ask doctor if - condition worsens- symptoms

last more then 7 days

KEEP OUT OF REACH OF CHILDREN:

In case of overdose, or accidental poisoning,

get medical help or contact a Poison Control Center right away.

DIRECTIONS:

Adults and children 12 years or older. Shake well.

DOSAGE AND ADMINISTRATION

Direct nozzel to sore throat area and spray 3-4 times.
Do not swallow.
Hold for 15 seconds or longer then spit remaining liquid out.

Other Ingredients

Viracea (proprietary Echinacea purpurea extract). Methylparaben

Potassium Sorbate (natural preservative). Propylparaben , water (purified)

Stevia, Natural honey and lemon flavors.

Throat Releev Honey Lemon label